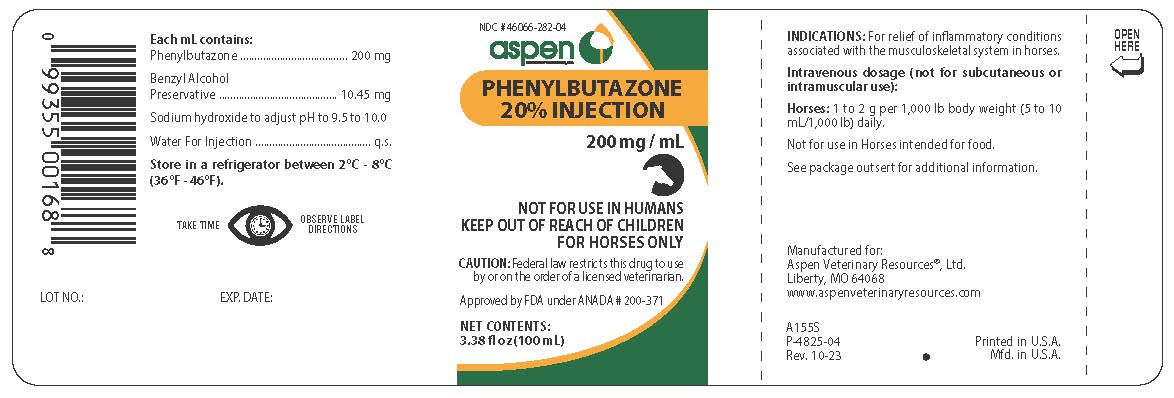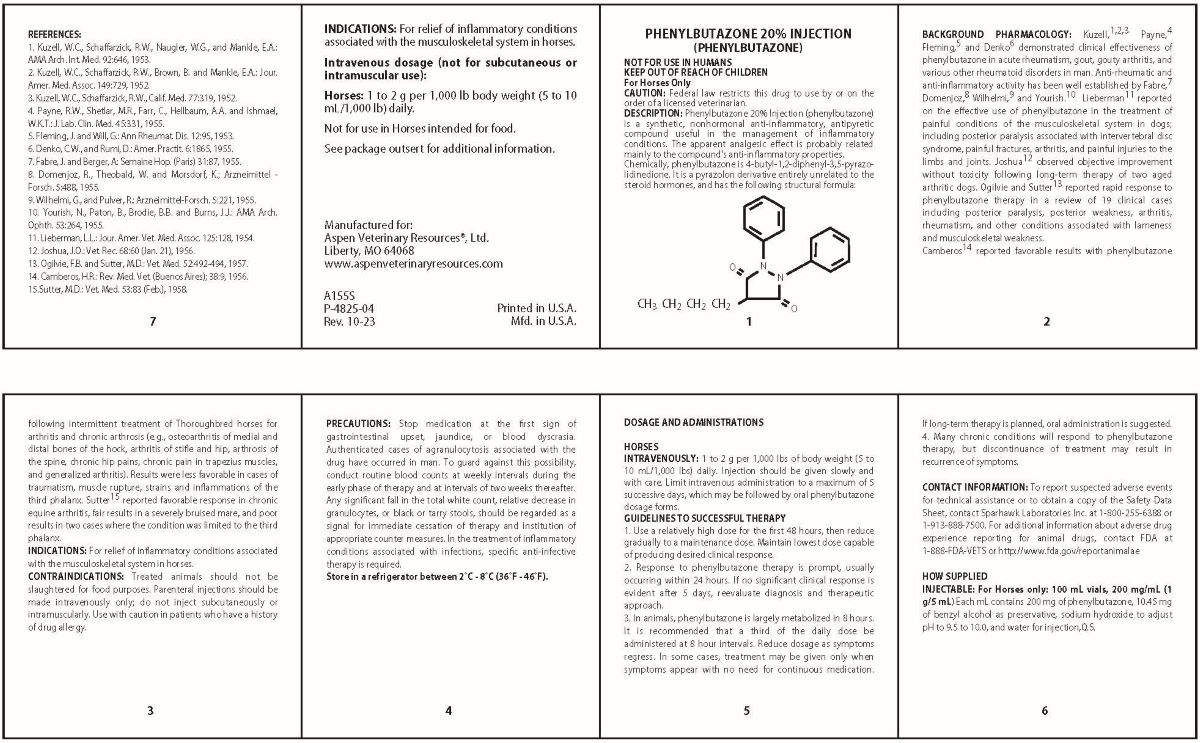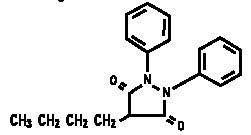 DRUG LABEL: PHENYLBUTAZONE 
NDC: 46066-282 | Form: INJECTION
Manufacturer: Aspen Veterinary Resources, Ltd.
Category: animal | Type: PRESCRIPTION ANIMAL DRUG LABEL
Date: 20240503

ACTIVE INGREDIENTS: PHENYLBUTAZONE 200 mg/1 mL
INACTIVE INGREDIENTS: BENZYL ALCOHOL; SODIUM HYDROXIDE

Phenylbutazone 20% Injection 200 mg/mL

GENERAL PRECAUTIONS

NOT FOR USE IN HUMANS

KEEP OUT OF REACH OF CHILDREN

FOR HORSES ONLY

CAUTION: Federal law restricts this drug to use by or on the order of a licensed veterinarian.

DESCRIPTION

DESCRIPTION: Phenylbutazone 20% Injection (phenylbutazone) is a synthetic, nonhormonal anti-inflammatory, antipyretic compound useful in the management of inflammatory conditions. The apparent analgesic effect is probably related mainly to the compound's anti-inflammatory properties. Chemically, phenylbutazone is 4-butyl-1,2-diphenyl-3,5-pyrazolidinedione. It is a pyrazolon derivative entirely unrelated to the steroid hormones, and has the following structural formula:

BACKGROUND PHARMACOLOGY

Kuzell,^(1, 2, 3) Payne,^4 Fleming,^5 and Denko^6 demonstrated clinical effectiveness of phenylbutazone in acute rheumatism, gout, gouty arthritis and various other rheumatoid disorders in man. Anti-rheumatic and anti-inflammatory activity has been well established by Fabre,^7 Domenjoz,^8 Wilhelmi,^9 and Yourish^10 Lieberman^11 reported on the effective use of phenylbutazone in the treatment of painful conditions of the musculoskeletal system in dogs; including posterior paralysis associated with intervertebral disc syndrome, painful fractures, arthritis, and painful injuries to the limbs and joints. Joshua^12 observed objective improvement without toxicity following long-term therapy of two aged arthritic dogs. Ogilvie and Sutter^13 reported rapid response to phenylbutazone therapy in a review of 19 clinical cases including posterior paralysis, posterior weakness, arthritis, rheumatism, and other conditions associated with lameness and musculoskeletal weakness.

Camberos^14 reported favorable results with phenylbutazone following intermittent treatment of Thoroughbred horses for arthritis and chronic arthrosis (e.g., osteoarthritis of medial and distal bones of the hock, arthritis of stifle and hip, arthrosis of the spine, chronic hip pains, achronic pain in the trapezius muscles, and generalized arthritis). Results were less favorable in cases of traumatism, muscle rupture, strains and inflammations of the third phalanx. Sutter^15 reported favorable response in chronic equine arthritis, fair results in a severely bruised mare, and poor results in two cases where the condition was limited to the third phalanx

INDICATIONS

For relief of inflammatory conditions associated with the musculoskeletal system in horses.

CONTRAINDICATIONS

Treated animals should not be slaughtered for food purposes. Parenteral injections should be made intravenously only; do not inject subcutaneously or intramuscularly. Use with caution in patients who have a history of drug allergy.

PRECAUTIONS

Stop medication at the first sign of gastrointestinal upset, jaundice, or blood dyscrasia. Authenticated cases of agranulocytosis associated with the drug have occurred in man. To guard against this possibility, conduct routine blood counts at weekly intervals of two weeks thereafter. Any significant fall in th total white count, relative decrease in granulocytes, or black or tarry stools, should be regarded as a signal for immediate cessation of therapy and institution of appropriate counter measures. In the treatment of inflammatory conditions associated with infections, specific anti-infective therapy is required.

STORAGE AND HANDLING

Store in refrigerator between 2°-8°C (36° - 46°F)

DOSAGE AND ADMINISTRATION

HORSES
INTRAVENOUSLY: 1 to 2 g per 1,000 lbs of body weight (5 to 10 mL/1,000 lbs) daily. Injection should be given slowly and with care. Limit intravenous administration to a maximum of 5 successive days, which may be followed by oral phenylbutazone dosage forms.

GUIDELINES TO SUCCESSFUL THERAPY
1. Use a relatively high dose for the first 48 hours, then reduce gradually to a maintenance dose. Maintain lowest dose capable of producing desired clinical response.
2. Response to phenylbutazone therapy is prompt, usually occurring within 24 hours. If no significant clinical response is evident after 5 days, reevaluate diagnosis and therapeutic approach.
3. In animals, phenylbutazone is largely metabolized in 8 hours. It is recommended that a third of the daily dose be administered at 8 hour intervals. Reduce dosage as symptoms regress. In some cases, treatment may be given only when symptoms appear with no need for continuous medication. If long-term therapy is planned, oral administration is suggested.
4. Many chronic conditions will respond to phenylbutazone therapy, but discontinuance of treatment may result in recurrence of symptoms.

CONTACT INFORMATION:

To report suspected adverse events
for technical assistance or to obtain a copy of the Safety Data
Sheet, contact Sparhawk Laboratories Inc. at 1-800-255-6388 or
1-913-888-7500. For additional information about adverse drug
experience reporting for animal drugs, contact FDA at
1-888-FDA-VETS or http://www.fda.gov/reportanimalae

HOW SUPPLIED

INJECTABLE: For Horses only: 100 mL vials, 200 mg/mL (1 g/5 mL) Each mL contians 200 mg of phenylbutazone, 10.45 mg of benzyl alcohol as preservative, sodium hydroxide to adjust pH to 9.5 to 10.0, and water for injection, Q.S.

REFERENCES

1. Kuzell, W.C., Schaffarzick, R.W., Naugler, W.G., and Mankle, E.A.: AMA Arch. Int. Med. 92:646, 1953.
2. Kuzell, W.C., Schaffarzick, R.W., Brown, B. and Mankle, E.A.: Jour. Amer. Med. Assoc. 149:729, 1952.
3. Kuzell, W.C., Schaffarzick, R.W., Calif. Med. 777:319, 1952.
4. Payne, R.W., Shetlar, M.R., Farr, C., Hellbaum, A.A., and Ishmael, W.K.T.: J.Lab. Clin. Med. 45:331, 1955.
5. Fleming, J. and @Will, G.: Ann Rheumat. Dis. 12:95, 1953.
6. Denko, C.W., and Rumi, D.: Amer. Practit. 6:1865, 1955.
7. Fabre, J. and Berger, A.: Semaine Hop. (Paris) 31:87, 1955.
8. Domenjoz, R., Theobald, W. and Morsdorf, K., Arzneimittel-Forsch. 5:488, 1955.
9 Wilhelmi, G., and Pulver, R.: Arzneimittel-Forsch. 5:221, 1955.
10. Yoursh, N., Paton, B., Brodie, B.B and Burns, J.J.: AMA Arch. Ophth. 53:264, 1955.
11. Lieberman, L.L.: Jour. Amer. Vet. Med. Assoc. 125:128, 1954.
12. Joshua, J.O.: Vet. Rec. 68:60 (Jan 21), 1956.
13. Ogilvie, F.B. and Sutter, M.D.: Vet. Med 52:492-494, 1957.
14. Camberos, H.R.: Rev. Med. Vet. (Buenos Aires); 38:9, 1956.
15. Sutter, M.F.: Vet Med. 53:83 (Feb.), 1958.

ROUTE, METHOD AND FREQUENCY OF ADMINISTRATION

INDICATIONS: For relief of inflammatory conditions associated with the musculoskeletal system in horses.

Intravenous dosage (not for subcutaneous or intramuscular use):
Horses: 1 to 2 g per 1,000 lb body weight (5 to 10 mL/1,000 lb) daily.

Not for use in Horses intended for food.

See package outsert for additional information.